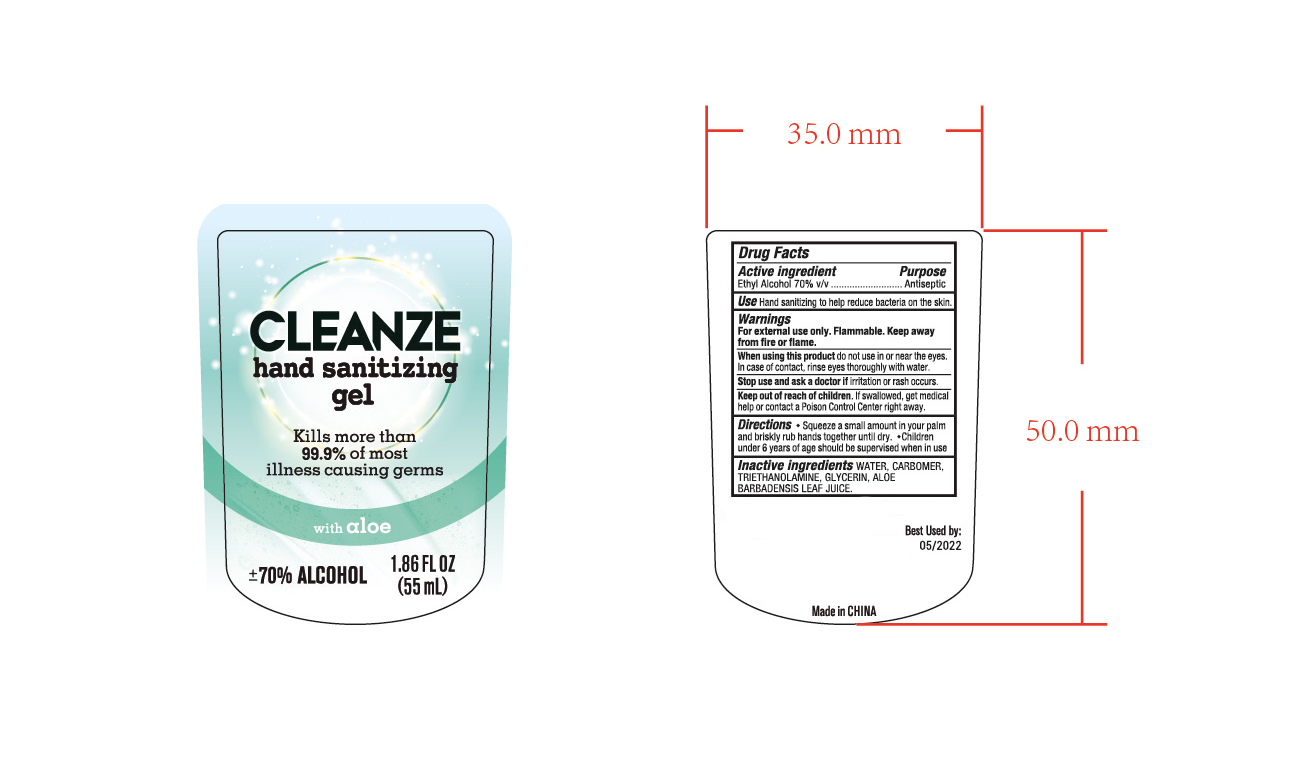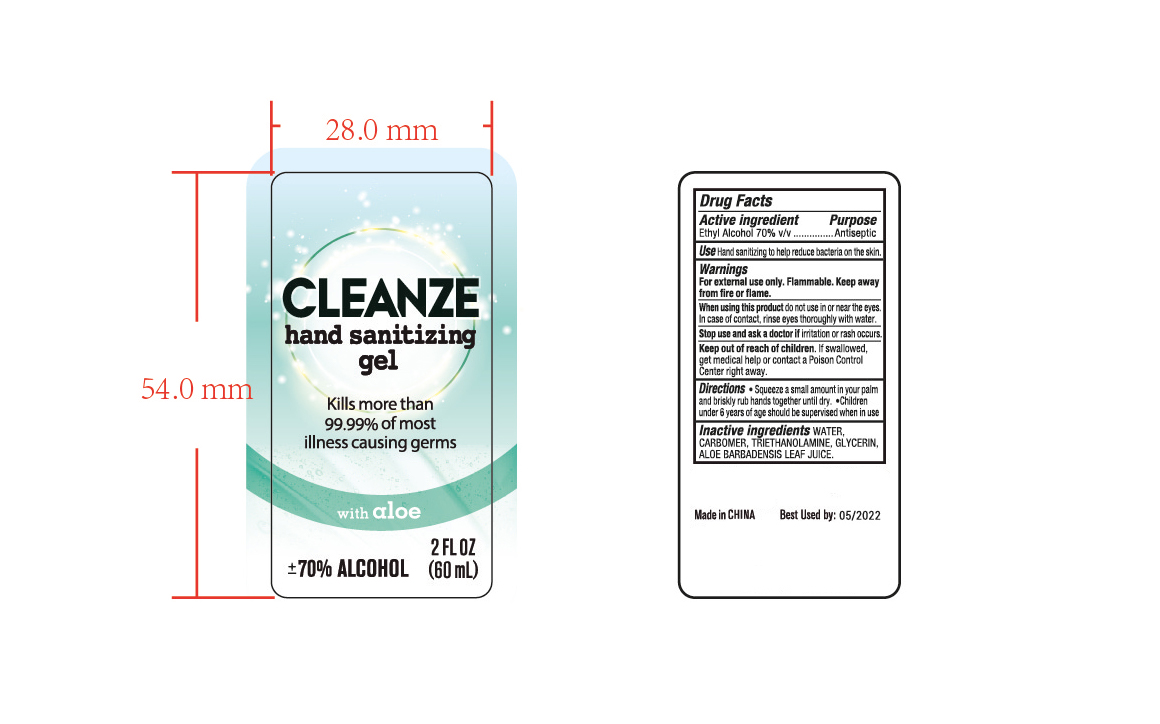 DRUG LABEL: HAND SANITIZER
NDC: 47993-266 | Form: GEL
Manufacturer: NINGBO JIANGBEI OCEAN STAR TRADING CO.,LTD
Category: otc | Type: HUMAN OTC DRUG LABEL
Date: 20201104

ACTIVE INGREDIENTS: ALCOHOL 70 mL/100 mL
INACTIVE INGREDIENTS: CARBOMER 940; GLYCERIN; TRIETHANOLAMINE BENZOATE; ALOE VERA LEAF; WATER

47993-266

Active ingredients

Ethyl Alcohol 70% v/v

PURPOSE

Antiseptic

Uses：

Hand sanitizing to help reduce bacteria on the skin.

Warnings:

For external use only. Flammable. Keep away from fire or flame.

When using this product do not use in or near the eyes. In case of contact， rinse eyes thoroughly with water.

Stop use and ask a doctor if irritation or rash occurs.

Keep out of reach of children. If swallowed，get medical help or contact a Poison Control Center right away.

Directions:

- Squeeze a small amount in your palm and briskly rub hands together until dry.
- Children under 6 years of age should be supervised when in use.

Inactive Ingredients:

Water,Carbomer,Triethanolamine,Glycerin,Aloe Barbadensis Leaf Juice